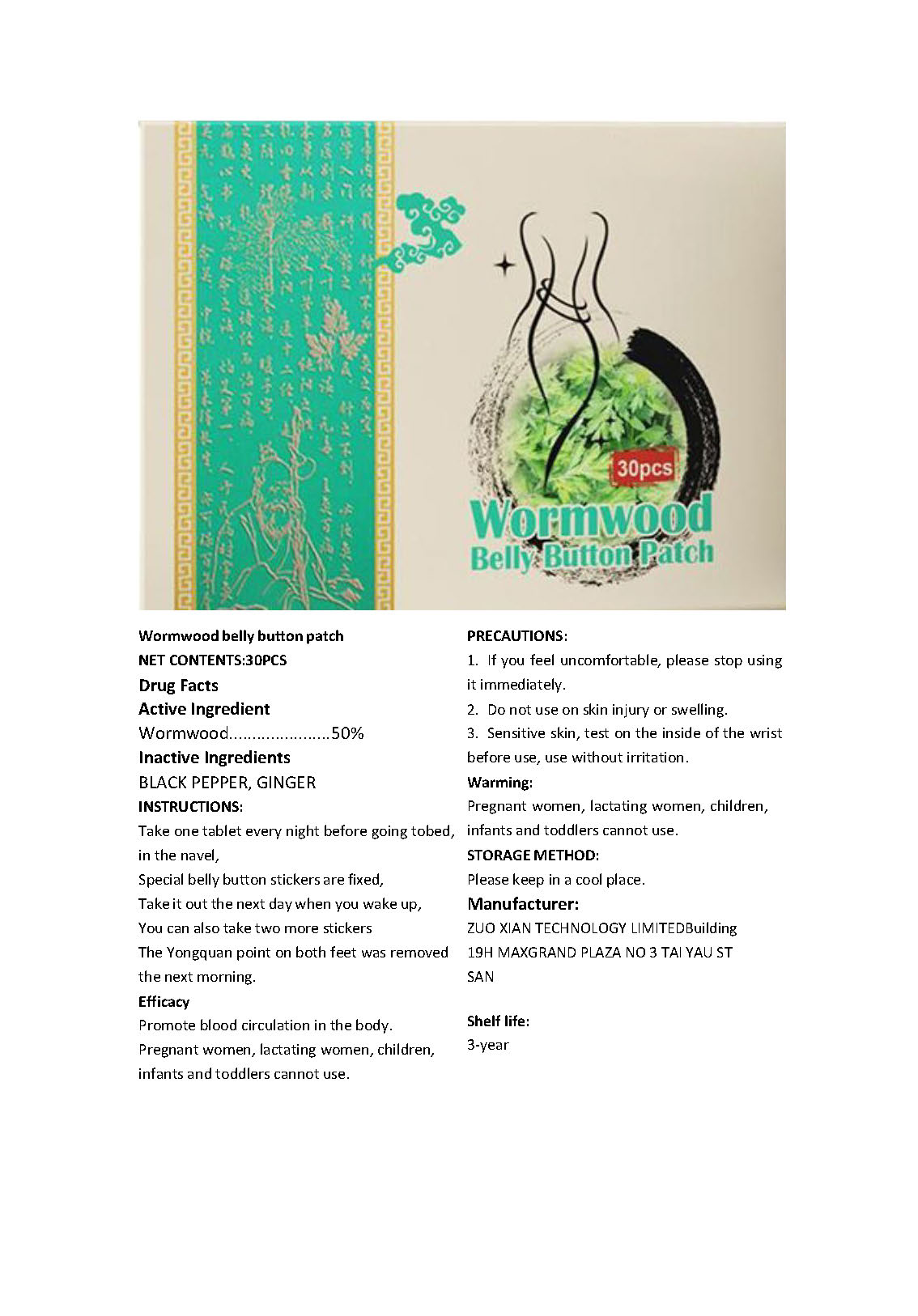 DRUG LABEL: Wormwood belly button patch
NDC: 84715-001 | Form: PATCH
Manufacturer: ZUO XIAN TECHNOLOGY LIMITED
Category: otc | Type: HUMAN OTC DRUG LABEL
Date: 20240905

ACTIVE INGREDIENTS: WORMWOOD 0.5 g/1 1
INACTIVE INGREDIENTS: BLACK PEPPER; GINGER

Wormwood belly button patch

ACTIVE INGREDIENT

WORMWOOD 50%

PURPOSE

Promote blood circulation in the body

INDICATIONS AND USAGE

Promote blood circulation in the body

KEEP OUT OF REACH OF CHILDREN

Pregnant women, lactating women, childreninfants and toddlers cannot use.

WARNINGS

Pregnant women, lactating women, childreninfants and toddlers cannot use.
For external use only

DOSAGE AND ADMINISTRATION

Take one tablet every night before going tobed
in the navel,
Special belly button stickers are fixed, Take it out the next day when you wake up,You can also take two more stickers
The Yongquan point on both feet was removedthe next morning

STORAGE AND HANDLING

Please keep in a cool place.

Shelf life:3-year

WHEN USING

3. Sensitive skin,test on the inside of the wristbefore use, use without irritation.

DO NOT USE

2. Do not use on skin injury or swelling

STOP USE

1. lf you feel uncomfortable, please stop usingit immediately.

INACTIVE INGREDIENT

BLACK PEPPER
GINGER